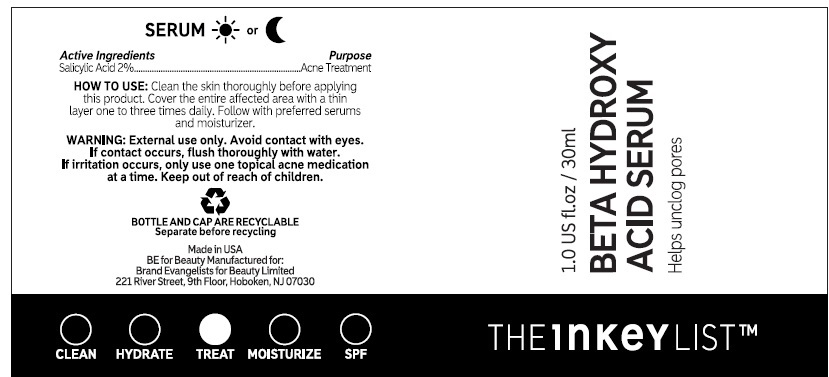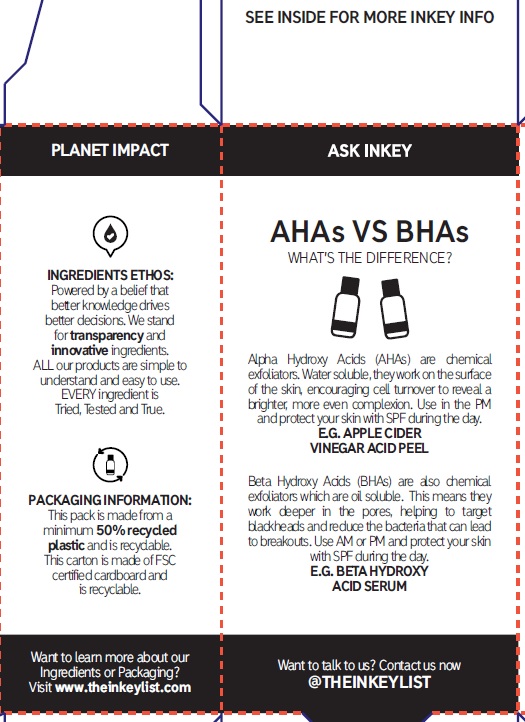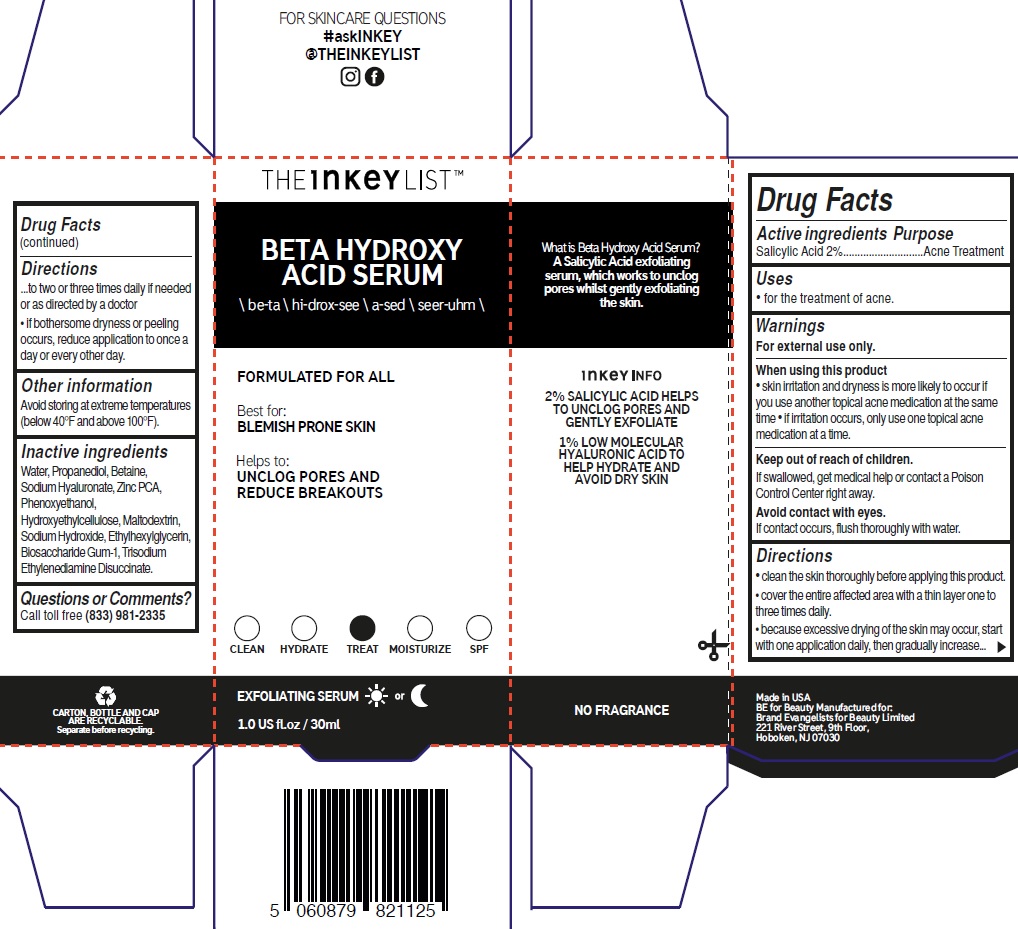 DRUG LABEL: The INKEY List Beta Hydroxy Acid Serum
NDC: 81136-021 | Form: GEL
Manufacturer: Brand Evangelists for Beauty Ltd
Category: otc | Type: HUMAN OTC DRUG LABEL
Date: 20240226

ACTIVE INGREDIENTS: SALICYLIC ACID 20 mg/1 mL
INACTIVE INGREDIENTS: PROPANEDIOL; WATER; BETAINE; HYALURONATE SODIUM; ZINC PIDOLATE; PHENOXYETHANOL; HYDROXYETHYL CELLULOSE, UNSPECIFIED; MALTODEXTRIN; SODIUM HYDROXIDE; ETHYLHEXYLGLYCERIN; BIOSACCHARIDE GUM-1; TRISODIUM ETHYLENEDIAMINE DISUCCINATE

The INKEY List Beta Hydroxy Acid Serum

Active ingredients

Salicylic Acid 2%

Purpose

Acne Treatment

Uses

• for the treatment of acne.

Warnings

For external use only.

When using this product

• skin irritation and dryness is more likely to occur if you use another topical acne medication at the same time • if irritation occurs, only use one topical acne medication at a time.

Keep out of reach of children.

If swallowed, get medical help or contact a Poison Control Center right away.

If contact occurs, flush thoroughly with water. Avoid contact with eyes.

Directions

• clean the skin thoroughly before applying this product. • cover the entire affected area with a thin layer one to three times daily. • because excessive drying of the skin may occur, start with one application daily, then gradually increase to two or three times daily if needed or as directed by a doctor • if bothersome dryness or peeling occurs, reduce application to once a day or every other day.

Other information

Avoid storing at extreme temperatures (below 40°F and above 100°F).

Inactive ingredients

Water, Propanediol, Betaine, Sodium Hyaluronate, Zinc PCA, Phenoxyethanol, Hydroxyethylcellulose, Maltodextrin, Sodium Hydroxide, Ethylhexylglycerin, Biosaccharide Gum-1, Trisodium Ethylenediamine Disuccinate.

Questions or Comments?

Call toll free (833) 981-2335